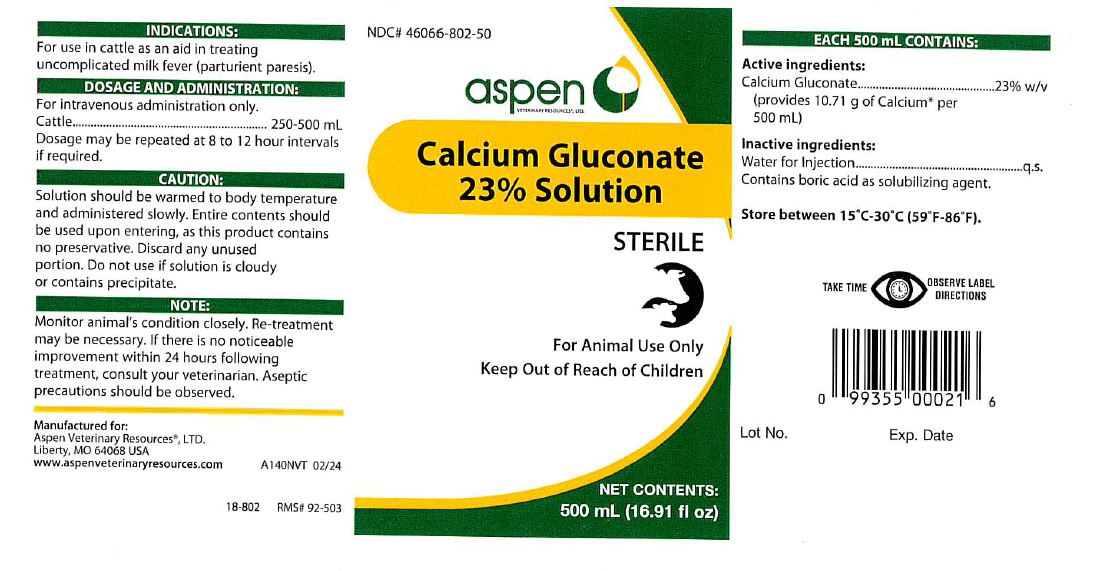 DRUG LABEL: Calcium Gluconate 23% Solution
NDC: 46066-802 | Form: INJECTION, SOLUTION
Manufacturer: Aspen Veterinary
Category: animal | Type: OTC ANIMAL DRUG LABEL
Date: 20241030

ACTIVE INGREDIENTS: Calcium Gluconate 23 g/100 mL

Calcium Gluconate 23% Solution

GENERAL PRECAUTIONS

For Animal Use Only

Keep Out of Reach of Children

INFORMATION FOR OWNERS/CAREGIVERS

NET CONTENTS: 500 mL (16.91 fl oz)

INDICATIONS:

For use in cattle as an aid in treating
uncomplicated milk fever (parturient paresis).

DOSAGE AND ADMINISTRATION:

For intravenous administration only.
Cattle...............250-500 mL
Dosage may be repeated at 8 to 12 hour intervals
if required.

CAUTION:

Solution should be warmed to body temperature
and administered slowly. Entire contents should
be used upon entering, as this product contains
no preservative. Discard any unused
portion. Do not use if solution is cloudy
or contains precipitate.

NOTE:

Monitor animal's condition closely. Re-treatment
may be necessary. If there is no noticeable
improvement within 24 hours following
treatment, consult your veterinarian. Aseptic
precautions should be observed.

EACH 500 mL CONTAINS:

Active Ingrdients:

Calcium Gluconate................23% w/v
(provides 10.71 g of Calcium* per
500 mL)

Inactive ingredients:

Water for Injection.......................q.s.
Contains boric acid as solubilizing agent.

STORAGE AND HANDLING

Store between 15°C - 30°C (59°F - 86°F).

INFORMATION FOR OWNERS/CAREGIVERS

STERILE

Manufactured for:
Aspen Veterinary ResourcesR ,Ltd.
Liberty, MO 64068 USA

www. aspenveterinaryresources.com A140NVT 02/24

18-802 RMS# 92-503

Lot No. Exp. Date

NDC# 46066-802-50

PRECAUTIONS

TAKE TIME OBSERVE LABEL DIRECTIONS